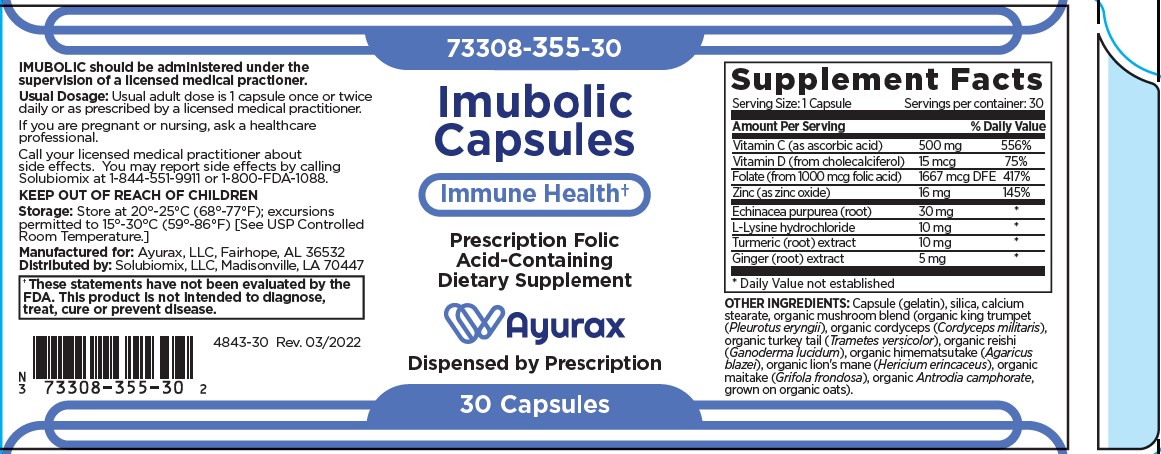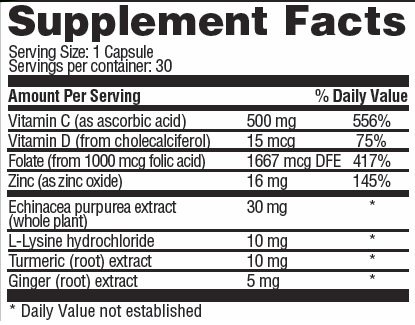 DRUG LABEL: IMUBOLIC
NDC: 73308-355 | Form: CAPSULE
Manufacturer: Ayurax
Category: other | Type: DIETARY SUPPLEMENT
Date: 20251006

ACTIVE INGREDIENTS: ASCORBIC ACID 500 mg/1 1; cholecalciferol 0.015 mg/1 1; ZINC OXIDE 16 mg/1 1; FOLIC ACID 1 mg/1 1; ECHINACEA PURPUREA WHOLE 30 mg/1 1; LYSINE HYDROCHLORIDE 10 mg/1 1; TURMERIC 10 mg/1 1; GINGER 5 mg/1 1
INACTIVE INGREDIENTS: GELATIN; CALCIUM STEARATE; SILICA DIMETHYL SILYLATE; PLEUROTUS ERYNGII WHOLE; TRAMETES VERSICOLOR WHOLE; CORDYCEPS MILITARIS WHOLE; GANODERMA LUCIDUM WHOLE; AGARICUS BLAZEI WHOLE; HERICIUM AMERICANUM WHOLE; TAIWANOFUNGUS CAMPHORATUS WHOLE; GRIFOLA FRONDOSA WHOLE

IMUBOLIC

HEALTH CLAIM:

IMUBOLIC Capsules - Dietary Supplement

Dispensed by Prescription‡

OTHER INGREDIENTS: gelatin, calcium stearate, silica, organic mushroom (Pleurotus eryngii), organic turkey tail (Trametes versicolor), organic cordyceps (Cordyceps militaris), organic reishi (Ganoderna lucidum) organic himematsutake (Agaricus blazei), organic lion's mane (Hericium erincaces), organic antrodia (Taiwanofungus camphoratus (Antrodia camphorate) , organic maitake (Grifola frondosa)

DESCRIPTION:

IMUBOLIC is an orally administered prescription vitamin formulation for the clinical dietary management of suboptimal nutritional status in patients where advanced supplementation is required and nutritional supplementation in physiologically stressful conditions for maintenance of good immune health is needed.†

IMUBOLIC is manufactured in accordance with Current Good Manufacturing Practice for foods, using ingredients that have been approved by the U.S. Food and Drug Administration (FDA) as food additives or are “Generally Recognized as Safe” (GRAS) for their intended use.

IMUBOLIC should be administered under the supervision of a licensed medical practitioner.

† These statements have not been evaluated by the Food and Drug Administration. This product is not intended to diagnose, treat, cure or prevent disease.

WARNING AND PRECAUTIONS

This product is contraindicated in patients with a known hypersensitivity to any of the ingredients. IMUBOLIC capsules should only be used under the direction and supervision of a licensed medical practitioner.‡ Use with caution in patients that may have a medical condition, are pregnant, lactating, trying to conceive, under the age of 18, or taking medications.

KEEP OUT OF REACH OF CHILDREN

PRECAUTION
Folic acid alone is improper therapy in the treatment of pernicious anemia and other megaloblastic anemias where vitamin B is deficient. Folic acid in doses above 1 mg daily may obscure pernicious anemia in that hematologic remission can occur while neurological manifestations progress. IMUBOLIC capsules should only be used under the direction and supervision of a licensed medical practitioner.

ADVERSE REACTIONS

Allergic sensitization has been reported following both oral and parenteral administration of folic acid. You may report side effects by calling 1-844-551-9911 or the FDA by calling 1-800-FDA-1088.

DOSAGE & ADMINISTRATION

Usual adult dose is 1 capsule taken orally once or twice daily or as prescribed by a licensed medical practitioner.

HOW SUPPLIED HEALTH CLAIM:

IMUBOLIC Dietary Supplement
Capsules are clear with a yellow powder inside
Bottles contain 30 capsules, 73308-355-30*
Dispensed by Prescription‡

Manufactured in USA for:

Ayurax, LLC

Fairhope, AL 36532

Distributed by: Solubiomix, LLC
Rev. 03/2022

* Ayurax does not represent these product codes to be National Drug Codes (NDC). Product codes are formatted according to standard industry practice, to meet the formatting requirement by pedigree reporting and supply-chain control including pharmacies.

‡ The most appropriate way to ensure pedigree reporting consistent with these regulatory guidelines and safety monitoring is to dispense this product by prescription. This is not an Orange Book product. This product may be administered only under a physician’s supervision and all prescriptions using this product shall be pursuant to state statutes as applicable. The ingredients, indication or claims of this product are not to be construed to be drug claims.

1. Federal Register Notice of August 2, 1973 (38 FR 20750)
2. Federal Register Notice of October 17, 1980 (45 FR 69043, 69044)
3. Federal Register Notice of March 5, 1996 (61 FR 8760)

STORAGE AND HANDLING:

STORAGE: Store at 20°-25°C (68°-77°F); excursions permitted to 15°-30°C (59°-86°F) [See USP]